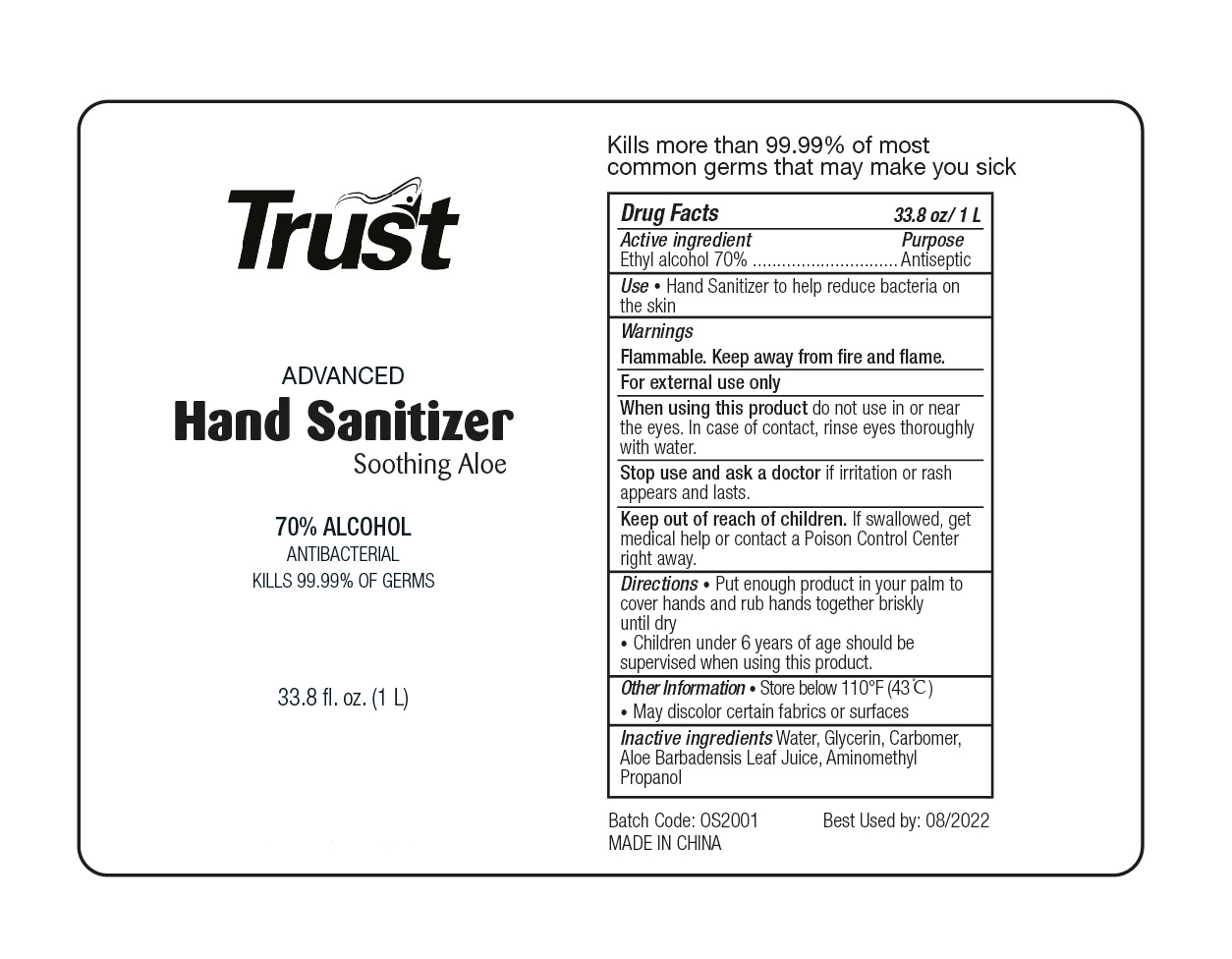 DRUG LABEL: HAND SANITIZER
NDC: 47993-298 | Form: GEL
Manufacturer: NINGBO JIANGBEI OCEAN STAR TRADING CO.,LTD
Category: otc | Type: HUMAN OTC DRUG LABEL
Date: 20201105

ACTIVE INGREDIENTS: ALCOHOL 70 g/112 mL
INACTIVE INGREDIENTS: WATER; GLYCERIN; CARBOMER 940; ALOE VERA LEAF; AMINOMETHYLPROPANOL

47993-298

Active ingredients

Ethyl Alcohol 70%

PURPOSE

Antiseptic

Uses：

Hand sanitizer to reduce bacteria on the skin.

Warnings:

Flammable. Keep away from fire or flame.

For external use only.

When using this product do not use in or near the eye. In case of contact, rinse eyes thoroughly with water.

Stop use and ask a doctor if irritation or rash appears and lasts.

Keep out of reach of children. If swallowed, get medical help or contact a Poison Control Center right away.

Directions:

- Put enough product in your palm to cover hands and rub hands together briskly until dry.
- Children under 6 years of age should be supervised when using this product.

Other information：

- Store below 110℉(43℃).
- May discolor certain fabrics or surfaces.

Inactive Ingredients:

Water,Glycerin,Carbomer,Aloe Barbadensis Leaf Juice,Aminomethyl Propanol.